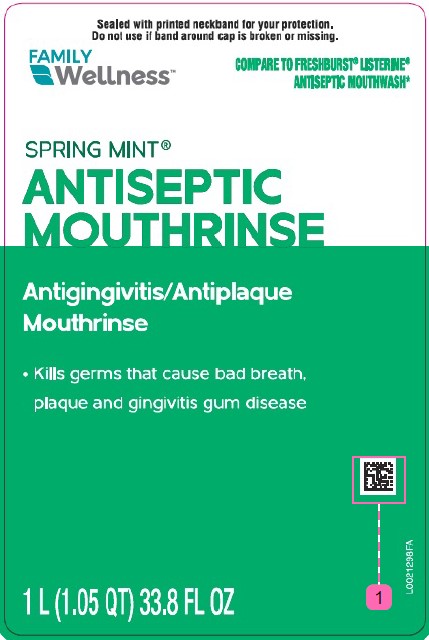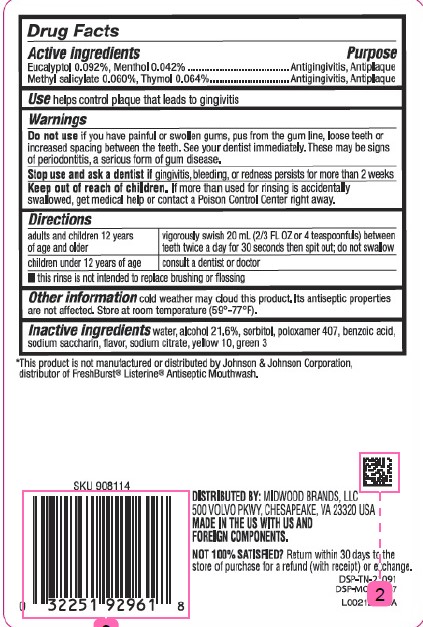 DRUG LABEL: Antiseptic Rinse Spring Mint
NDC: 55319-972 | Form: MOUTHWASH
Manufacturer: Family Dollar Stores, Inc
Category: otc | Type: HUMAN OTC DRUG LABEL
Date: 20260224

ACTIVE INGREDIENTS: EUCALYPTOL 0.92 mg/1 mL; MENTHOL 0.42 mg/1 mL; METHYL SALICYLATE 0.6 mg/1 mL; THYMOL 0.64 mg/1 mL
INACTIVE INGREDIENTS: WATER; ALCOHOL; SORBITOL; POLOXAMER 407; BENZOIC ACID; SACCHARIN SODIUM; SODIUM CITRATE; D&C YELLOW NO. 10; FD&C GREEN NO. 3

Family Wellness 072.003/072AL rev 2-072AN
Spring Mint Antiseptic Mouthrinse

Active ingredients

Eucalyptol 0.092%

Menthol 0.042%

Methyl salicylate 0.060%

Thymol 0.064%

Purpose

Antigingivitis, Antiplaque

Use

helps control plaque that leads to gingivitis

Warnings

for this product

Do not use

if you have painful or swollen gums, pus from the gum line, loose teeth or increased spacing between the teeth. See your dentist immediately. These may be signs of periodontitis, a serious form of gum disease.

Stop use and ask a dentist if

gingivitis, bleeding, or redness persists for more than 2 weeks

Keep out of reach of children.

If more than used for rinsing is accidentally swallowed, get medical help or contact a Poison Control Center right away.

Directions

adults and children 12 years of age and older - vigorously swish 20 ml (2/3 FL OZ or 4 teaspoonfuls) between teeth twice a day for 30 seconds then spit out; do not swallow

children under 12 years of age - consult a dentist or doctor

- this rinse is not intended to replace brushing or flossing

Other information

cold weather may cloud this product. Its antiseptic properties are not affected. Store at room temperature (59° -77°F).

Inactive ingredients

water, alcohol 21.6%, sorbitol, poloxamer 407, benzoic acid, sodium saccharin, flavor, sodium citrate, yellow no 10, green no 3

Disclaimer

*This product is not manufactured or distributed by Johnson & Johnson Corporation, distributor of FreshBurst®Listerine®Antiseptic Mouthwash.

Adverse Reaction

Distributed by Midwood Brands, LLC

500 VOLVO PKWY, CHESAPEAKE, VA 23320 USA

MADE IN THE US WITH US AND FOREIGN COMPONENTS.

NOT 100% SATISFIED? Return within 30 days to the store of purchase for a refund (with receipt) or exchange.

DSP-TN-21091

DSP-MO-20087

Principal Panel Display

Sealed With Printed Neckband For Your Protection

Do not use if band around cap is broken or missing.

FAMILY WELLNESS™

COMPARE TO FRESHBURST®LISTERINE®ANTISEPTIC MOUTHWASH*

SPRING MINT®

ANTISEPTIC

MOUTHRINSE

Antigingivitis/Antiplaque

Mouthrinse

- Kills germs that cause bad breath, plaque, gingivitis gum disease

1 L (1.05 QT) 33.8 FL OZ